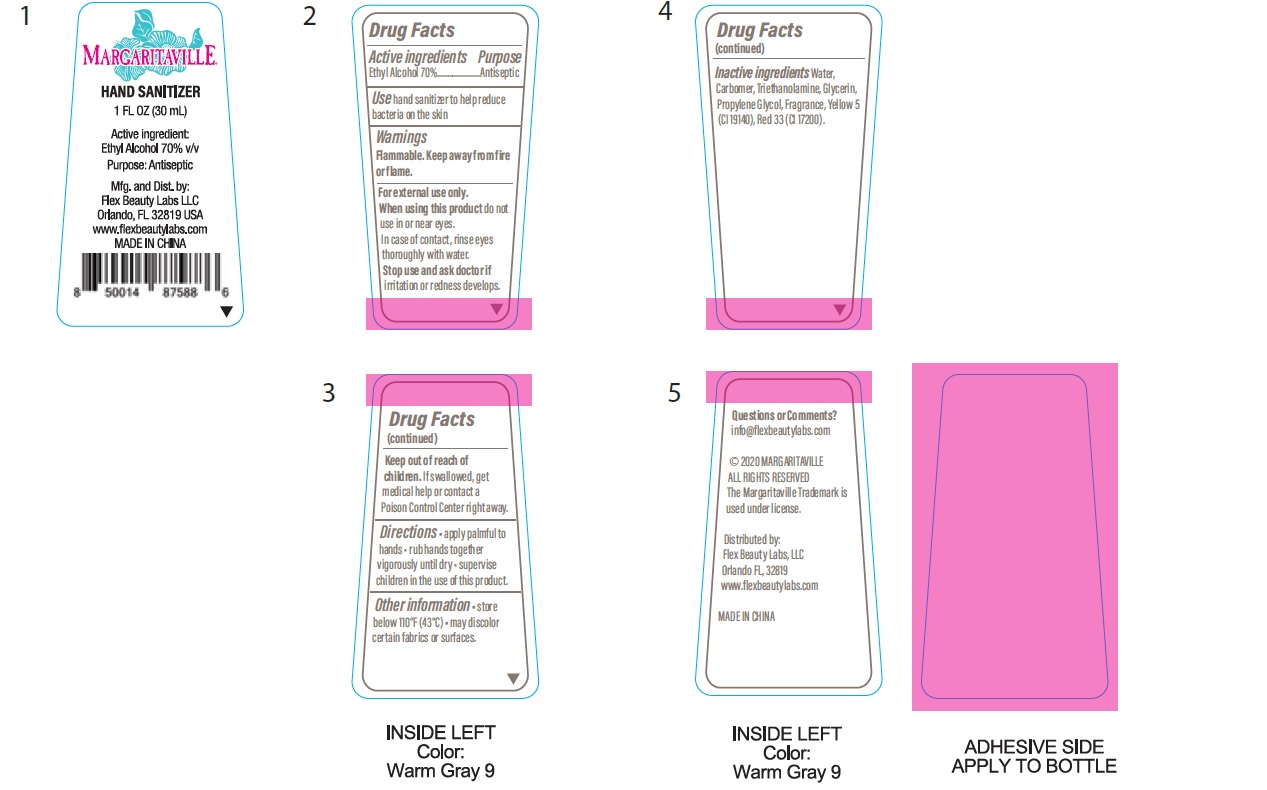 DRUG LABEL: Women to Blame

NDC: 72308-040 | Form: GEL
Manufacturer: Flex Beauty Labs
Category: otc | Type: HUMAN OTC DRUG LABEL
Date: 20210712

ACTIVE INGREDIENTS: ALCOHOL 0.7 mL/1 mL
INACTIVE INGREDIENTS: ALOE VERA LEAF; BASIC YELLOW 5; WATER; TROLAMINE; CARBOMER HOMOPOLYMER, UNSPECIFIED TYPE; PROPYLENE GLYCOL; GLYCERIN; .ALPHA.-TOCOPHEROL ACETATE

Margaritaville 1 Oz Pink Holder PInk Liquid Cherry Scent

Active Ingredients

Ethyl Alcohol 70% v/v.................Antiseptic

Purpose

Antiseptic

Use

hand sanitizer to help reduce bacteria on the skin

Safety Instructions

Flammable, Keep away from fire and flame

When using this product

In case of contact,rinse eyes thoroughly with water

Do not use in or near eyes.

KEEP OUT OF REACH OF CHILDREN

If swallowed, get medical help or contact Poison Control center right away.

Directions

- apply palmful to hands.
- rub hands together vigorously until dry.
- supervise children in the use of this product.

Other Information

Store below 110°F (43°C)
May discolor certain fabrics or surfaces.

Inactive Ingredients

Water, Carbomer, Triethanolamine, Glycerin, Propylene Glycol, Aloe Barbadensis Leaf Juice, Tocopheryl Acetate, Fragrance, Yellow 5 (CI19140), Red 33